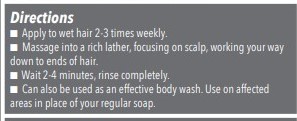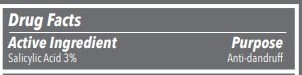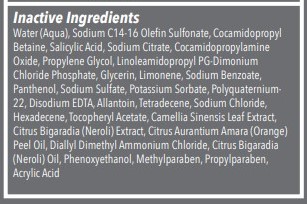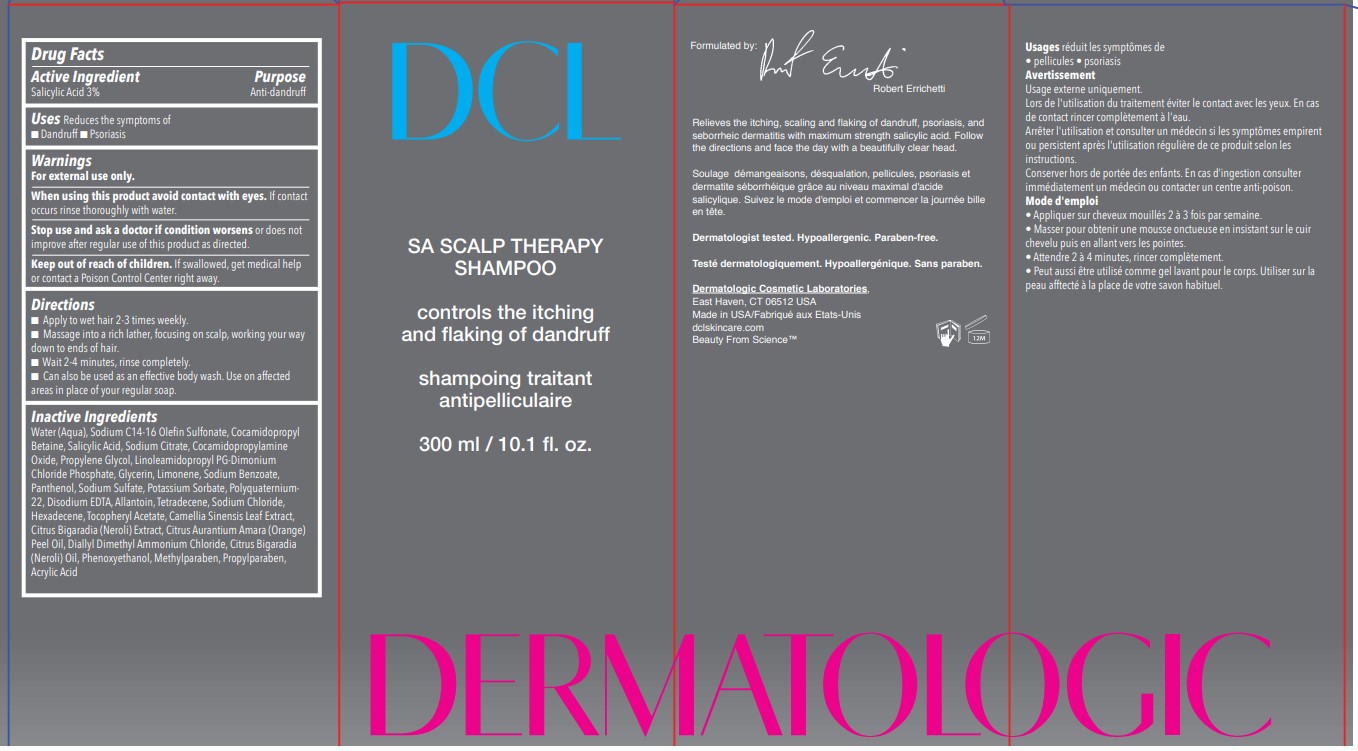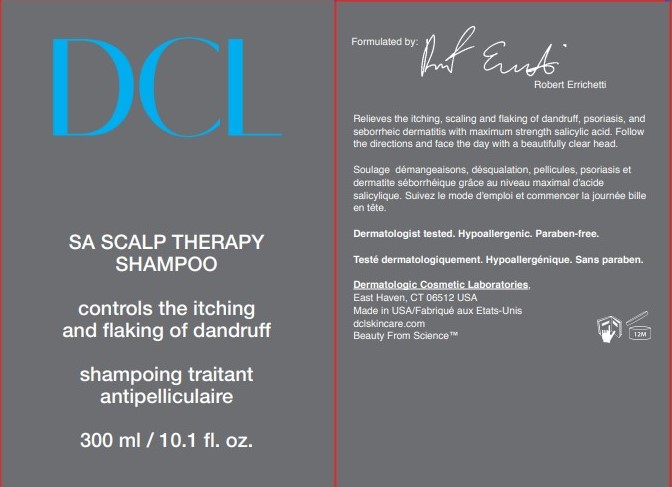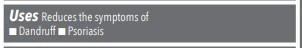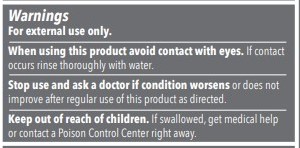 DRUG LABEL: SA Scalp Therapy
NDC: 57577-311 | Form: LOTION/SHAMPOO
Manufacturer: Milbar Laboratories
Category: otc | Type: HUMAN OTC DRUG LABEL
Date: 20250314

ACTIVE INGREDIENTS: SALICYLIC ACID 30 g/236 mL
INACTIVE INGREDIENTS: SODIUM CHLORIDE; PROPYLENE GLYCOL; WATER; SODIUM BENZOATE; CAMELLIA SINENSIS LEAF; ALLANTOIN; COCAMIDOPROPYL BETAINE; PHENOXYETHANOL; GLYCERIN; POLYQUATERNIUM-22 (4500 MPA.S); COCAMIDOPROPYL DIMETHYLAMINE; POTASSIUM SORBATE; EDETATE DISODIUM; PANTHENOL; ALPHA-TOCOPHEROL ACETATE; SODIUM C14-16 OLEFIN SULFONATE; METHYLISOTHIAZOLINONE; SODIUM SULFATE; SODIUM DICHLOROACETATE; LINOLEAMIDOPROPYL PG-DIMONIUM CHLORIDE PHOSPHATE; SODIUM CITRATE; COCAMIDOPROPYLAMINE OXIDE; METHYLCHLOROISOTHIAZOLINONE

SA Scalp